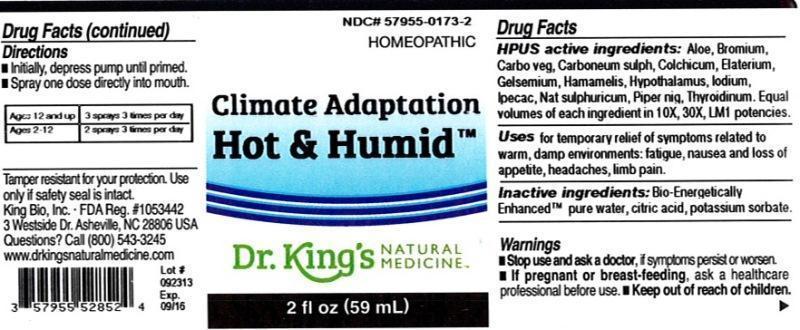 DRUG LABEL: Climate Adaptation Hot and Humid
NDC: 57955-0173 | Form: LIQUID
Manufacturer: King Bio Inc.
Category: homeopathic | Type: HUMAN OTC DRUG LABEL
Date: 20131119

ACTIVE INGREDIENTS: ALOE 10 [hp_X]/59 mL; BROMINE 10 [hp_X]/59 mL; ACTIVATED CHARCOAL 10 [hp_X]/59 mL; CARBON DISULFIDE 10 [hp_X]/59 mL; COLCHICUM AUTUMNALE BULB 10 [hp_X]/59 mL; ECBALLIUM ELATERIUM FRUIT 10 [hp_X]/59 mL; GELSEMIUM SEMPERVIRENS ROOT 10 [hp_X]/59 mL; HAMAMELIS VIRGINIANA ROOT BARK/STEM BARK 10 [hp_X]/59 mL; BOS TAURUS HYPOTHALAMUS 10 [hp_X]/59 mL; IODINE 10 [hp_X]/59 mL; IPECAC 10 [hp_X]/59 mL; SODIUM SULFATE 10 [hp_X]/59 mL; GREEN PEPPERCORN 10 [hp_X]/59 mL; THYROID, UNSPECIFIED 10 [hp_X]/59 mL
INACTIVE INGREDIENTS: WATER; CITRIC ACID MONOHYDRATE; POTASSIUM SORBATE

Climate Adaptation Hot and Humid™

ACTIVE INGREDIENT

Drug Facts__________________________________________________________________________________________________________

HPUS active ingredients: Aloe socotrina, Bromium, Carbo vegetabilis, Carboneum sulphuratum, Colchicum autumnale, Elaterium, Gelsemium sempervirens, Hamamelis virginiana, Hypothalamus, Iodium, Ipecacuanha, Natrum sulphuricum, Piper nigrum, Thyroidinum. Equal volumes of each ingredient in 10X, 30X, LM1 potencies.

INDICATIONS AND USAGE

Uses for temporary relief of symptoms related to warm, damp environments: fatigue, nausea and loss of appetite, headaches, limb pain.

Inactive Ingredients:

Bio-Energetically Enhanced™ pure water, citric acid and potassium sorbate.

Warnings

- Stop use and ask your doctor if symptoms persist or worsen.

- If pregnant or breast-feeding, ask a healthcare professional before use.

- Keep out of reach of children

DOSAGE AND ADMINISTRATION

- Initially, depress pump until primed.
- Spray one dose directly into mouth.
- Ages 12 and up- 3 sprays 3 times per day.
- Ages 2-12- 2 sprays 3 times per day.

OTHER SAFETY INFORMATION

Tamper resistant for your protection. Use only if safety seal is intact.

PURPOSE

Uses for temporary relief of symptoms related to warm, damp environments:

- fatigue
- nausea and loss of appetite
- headaches
- limb pain